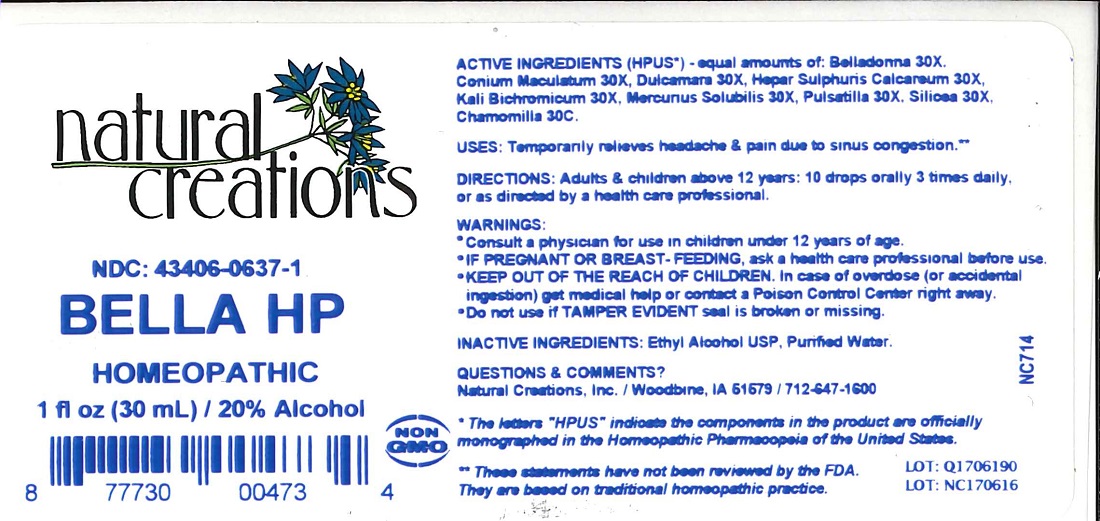 DRUG LABEL: BELLA HP
NDC: 43406-0637 | Form: LIQUID
Manufacturer: Natural Creations, Inc.
Category: homeopathic | Type: HUMAN OTC DRUG LABEL
Date: 20251113

ACTIVE INGREDIENTS: ATROPA BELLADONNA 30 [hp_X]/1 mL; CONIUM MACULATUM FLOWERING TOP 30 [hp_X]/1 mL; SOLANUM DULCAMARA TOP 30 [hp_X]/1 mL; CALCIUM SULFIDE 30 [hp_X]/1 mL; POTASSIUM DICHROMATE 30 [hp_X]/1 mL; MERCURIUS SOLUBILIS 30 [hp_X]/1 mL; ANEMONE PULSATILLA 30 [hp_X]/1 mL; SILICON DIOXIDE 30 [hp_X]/1 mL; MATRICARIA RECUTITA 30 [hp_C]/1 mL
INACTIVE INGREDIENTS: ALCOHOL; WATER

BELLA HP

ACTIVE INGREDIENT

ACTIVE INGREDIENTS (HPUS*) - equal amounts of: Belladonna 30X, Conium Maculatum 30X, Dulcamara 30X, Hepar Sulphuris Calcareum 30X, Kali Bichromicum 30X, Mercurius Solubilis 30X, Pulsatilla 30X, Silicea 30X, Chamomilla 30C.

PURPOSE

USES: Temporarily relieves headache & pain due to sinus congestion.**

INDICATIONS AND USAGE

USES: Temporarily relieves headache & pain due to sinus congestion.**

DOSAGE AND ADMINISTRATION

DIRECTIONS: Adults & children above 12 years: 10 drops orally 3 times daily, or as directed by a health care professional.

WARNINGS:

* Consult a physician for use in children under 12 years of age.

* IF PREGNANT OR BREAST-FEEDING, ask a health care professional before use.

* KEEP OUT OF THE REACH OF CHILDREN. In case of overdose (or accidental ingestion) get medical help or contact a Poison Control Center right away.

* Do not use if TAMPER EVIDENT seal is broken or missing.

KEEP OUT OF REACH OF CHILDREN

KEEP OUT OF THE REACH OF CHILDREN. In case of overdose (or accidental ingestion) get medical help or contact a Poison Control Center right away.

INACTIVE INGREDIENTS: Ethyl Alcohol USP, Purified Water.

QUESTIONS & COMMENTS?

Natural Creations, Inc. / Woodbine, IA 51579 / 712-647-1600

REFERENCES

* The letters "HPUS" indicate the components in the product are officially monographed in the Homeopathic Pharmacopeia of the United States.

** These statements have not been reviewed by the FDA. They are based on traditional homeopathic practice.

LOT:

PACKAGE LABEL

NDC: 43406-0637-1

BELLA HP

HOMEOPATHIC

1 fl oz (30 mL) / 20% Alcohol

UPC: 877730004734 NON GMO Logo